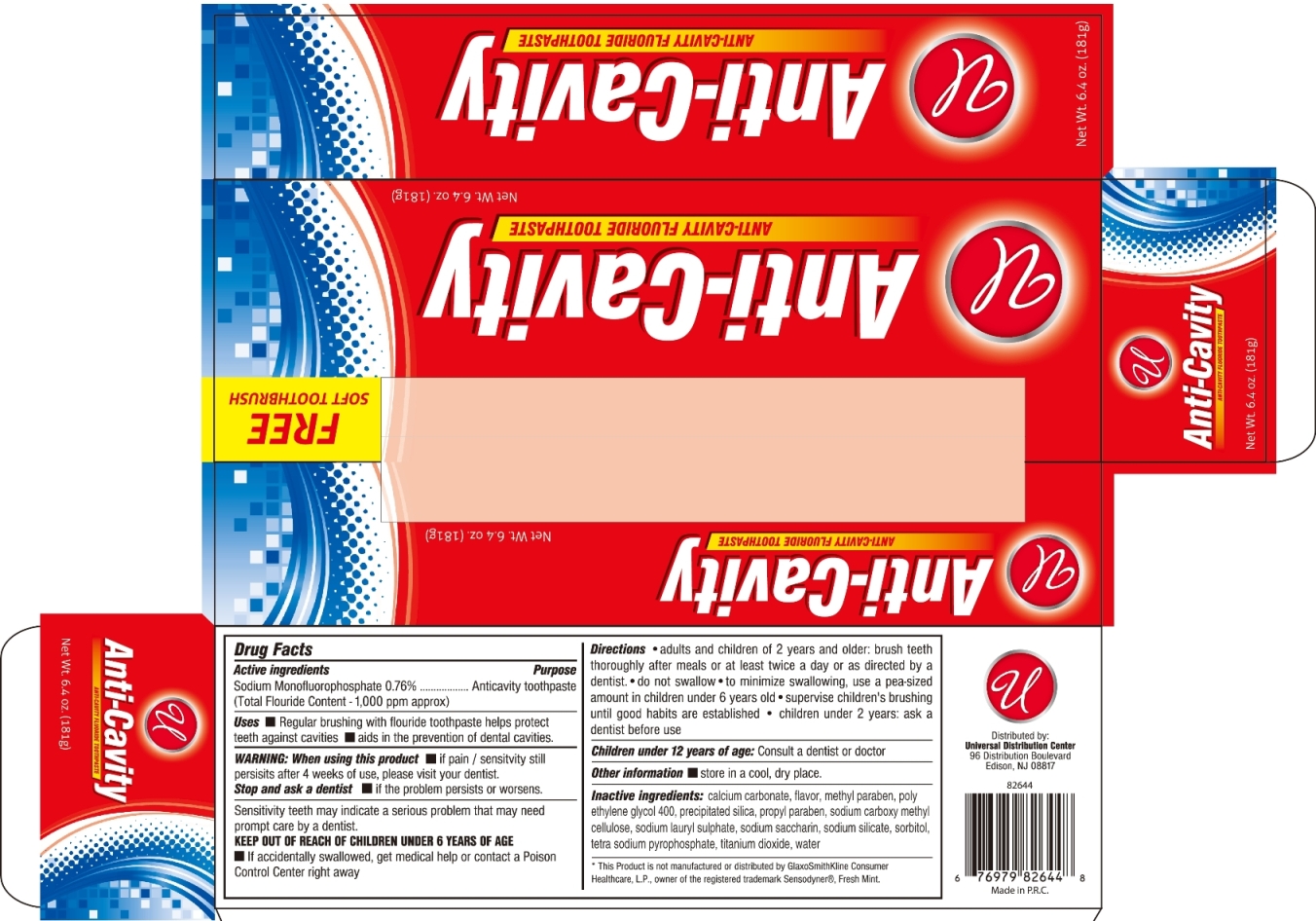 DRUG LABEL: ANTI CAVITY FLUORIDE
NDC: 52000-036 | Form: PASTE
Manufacturer: Universal Distribution Center LLC
Category: otc | Type: HUMAN OTC DRUG LABEL
Date: 20170621

ACTIVE INGREDIENTS: SODIUM MONOFLUOROPHOSPHATE 7.6 mg/1 g
INACTIVE INGREDIENTS: CALCIUM CARBONATE; METHYLPARABEN; POLYETHYLENE GLYCOL 400; PROPYLPARABEN; CARBOXYMETHYLCELLULOSE SODIUM, UNSPECIFIED FORM; SODIUM LAURYL SULFATE; SACCHARIN SODIUM; SODIUM SILICATE; SORBITOL; SODIUM PYROPHOSPHATE; TITANIUM DIOXIDE; WATER

ANTI-CAVITY FLUORIDE TOOTHPASTE

Active Ingredient

Sodium Monofluorophosphate 0.76%

(Total Fluoride Content - 1000 ppm approx.)

Purpose

Anticavity toothpaste

Uses

- regular brushing with flouride toothpaste helps protect teeth againts builds increasing protection against painful sensitivity of teeth due to cold, heat, acids, sweets or contact.
- aids in the prevention of dental cavities.

Warning

When using this product

- if pain\ sensitivity still persists after 4 weeks of use, please visit your dentist.

Stop and ask a dentist

- if the problem persists or worsens.

Sensitivity teeth may indicate a serious problem that may need prompt care by a dentist.

Keep out of reach of children under 6 years of age

- If accidentally swallowed get medical help or contact a Poison Control Center right away.

Directions

- adults and children of 6 years and older: brush teeth thoroughly, after meals or at least twice a day, or as directed by a dentist.
- do not swallow.
- to minimize swallowing, use pea-sized amount in children under 6 years old.
- supervise child's brushing until good habits are established.
- children under 2 years: ask a dentist before use.

Other information

- store in a cool, dry place.

Inactive Ingredients

calcium carbonate, flavor, methylparaben, poly ethylene glycol 400, precipited silica, propylparaben, sodium carboxymethyl cellulose, sodium lauryl sulfate, sodium saccharin, sodium silicate, sorbitol, tetra sodium pyrophosphate, titanium dioxide, water.

PACKAGE LABEL

PRINCIPAL DISPLAY PANEL

ANTI-CAVITY FLUORIDE TOOTHPASTE